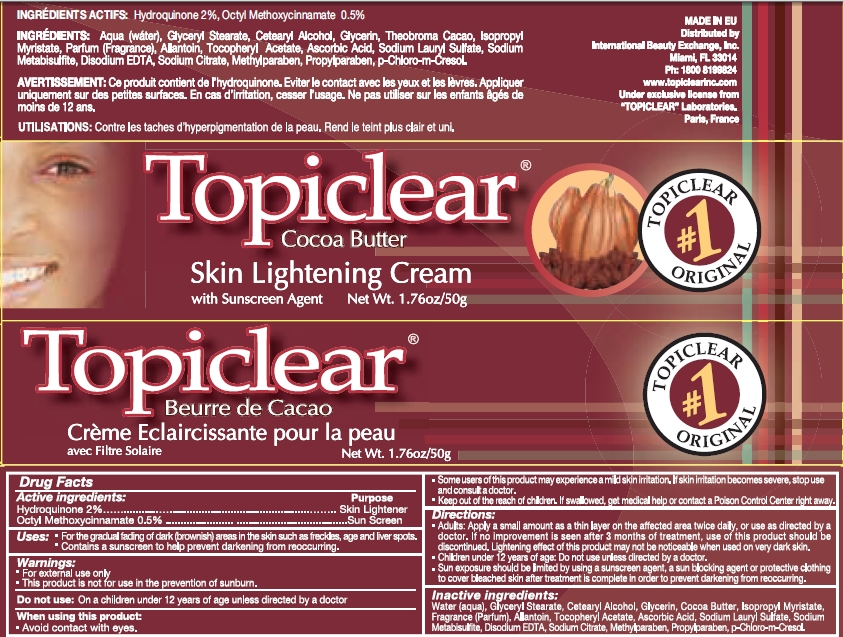 DRUG LABEL: Topiclear Cocoa Butter
NDC: 66129-012 | Form: CREAM
Manufacturer: International Beauty Exchange
Category: otc | Type: HUMAN OTC DRUG LABEL
Date: 20110525

ACTIVE INGREDIENTS: HYDROQUINONE 1 g/50 g; OCTINOXATE .25 g/50 g
INACTIVE INGREDIENTS: WATER; GLYCERYL STEARATE CITRATE; CETOSTEARYL ALCOHOL; GLYCERIN; ISOPROPYL MYRISTATE; ALLANTOIN; ASCORBIC ACID; SODIUM METABISULFITE; SODIUM CITRATE; SODIUM LAURYL SULFATE; EDETATE DISODIUM; METHYLPARABEN; PROPYLPARABEN; CHLOROCRESOL; COCOA BUTTER

Drug Facts

ACTIVE INGREDIENT

Hydroquinone 2%

Ethylhexyl Methoxycinnamate (Octyl Methoxycinnamate) 0.5%

WARNINGS

For external use only

DO NOT USE

On children under 12 years of age unless directed by a doctor

WHEN USING

Avoid contact with eyes.

PURPOSE

Skin Lightener